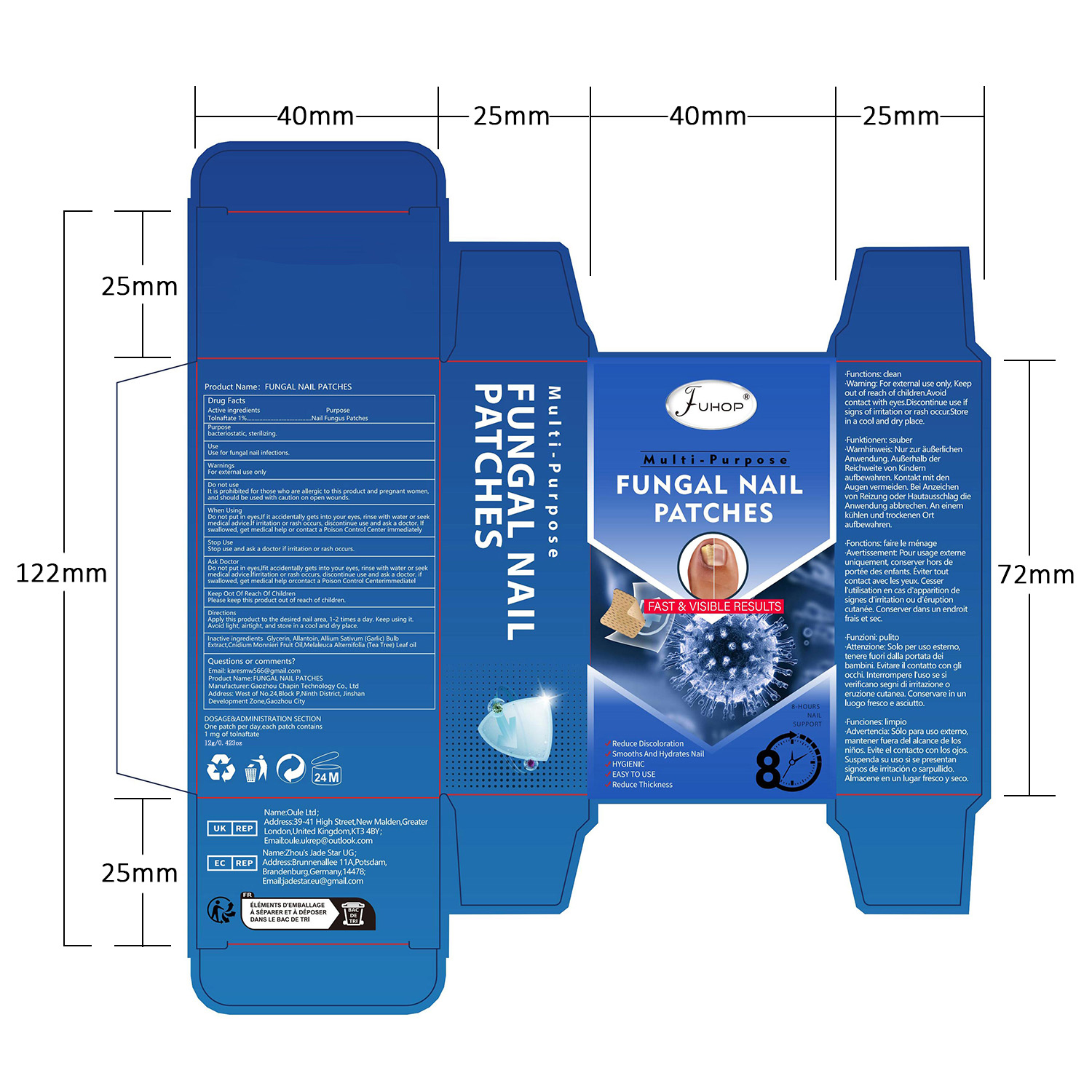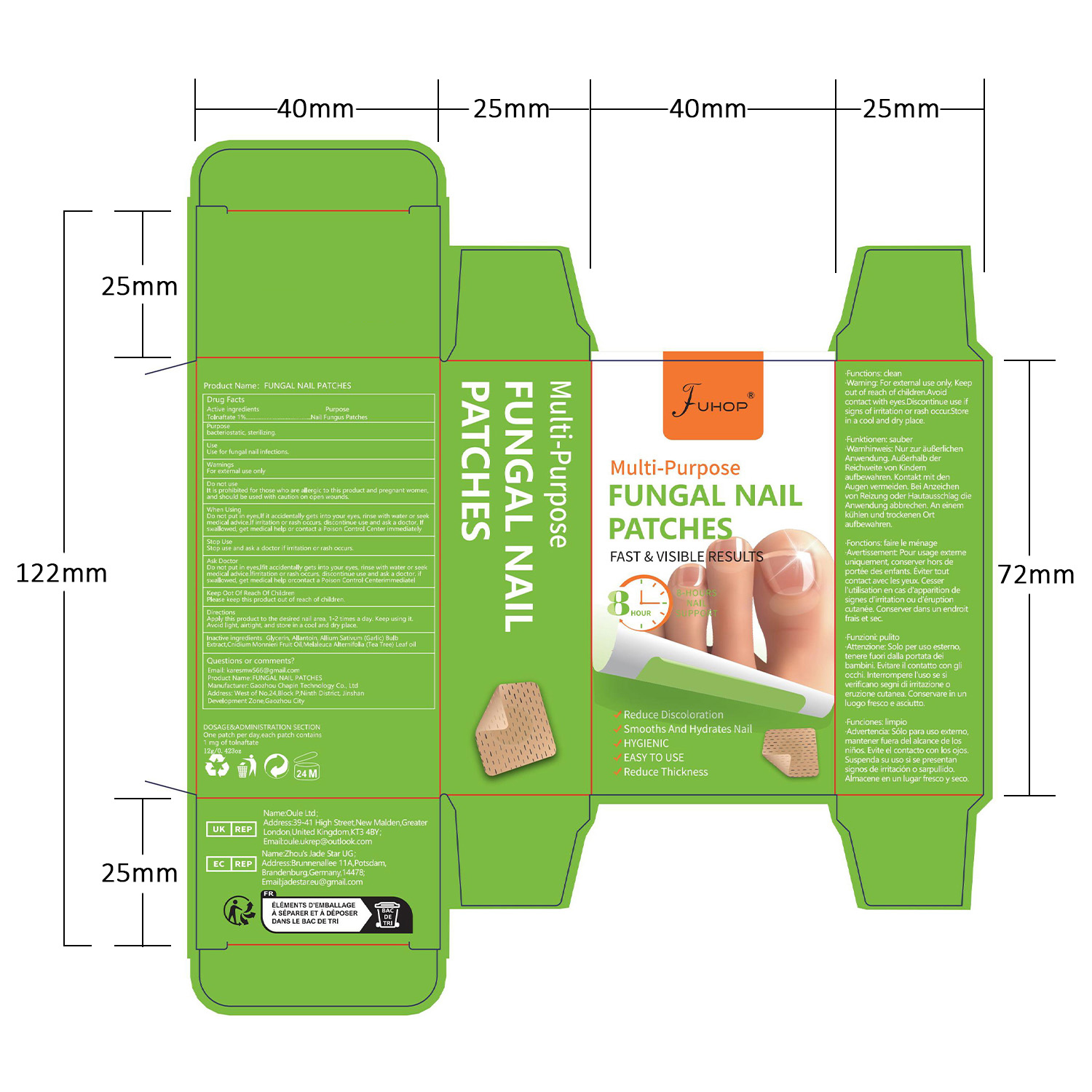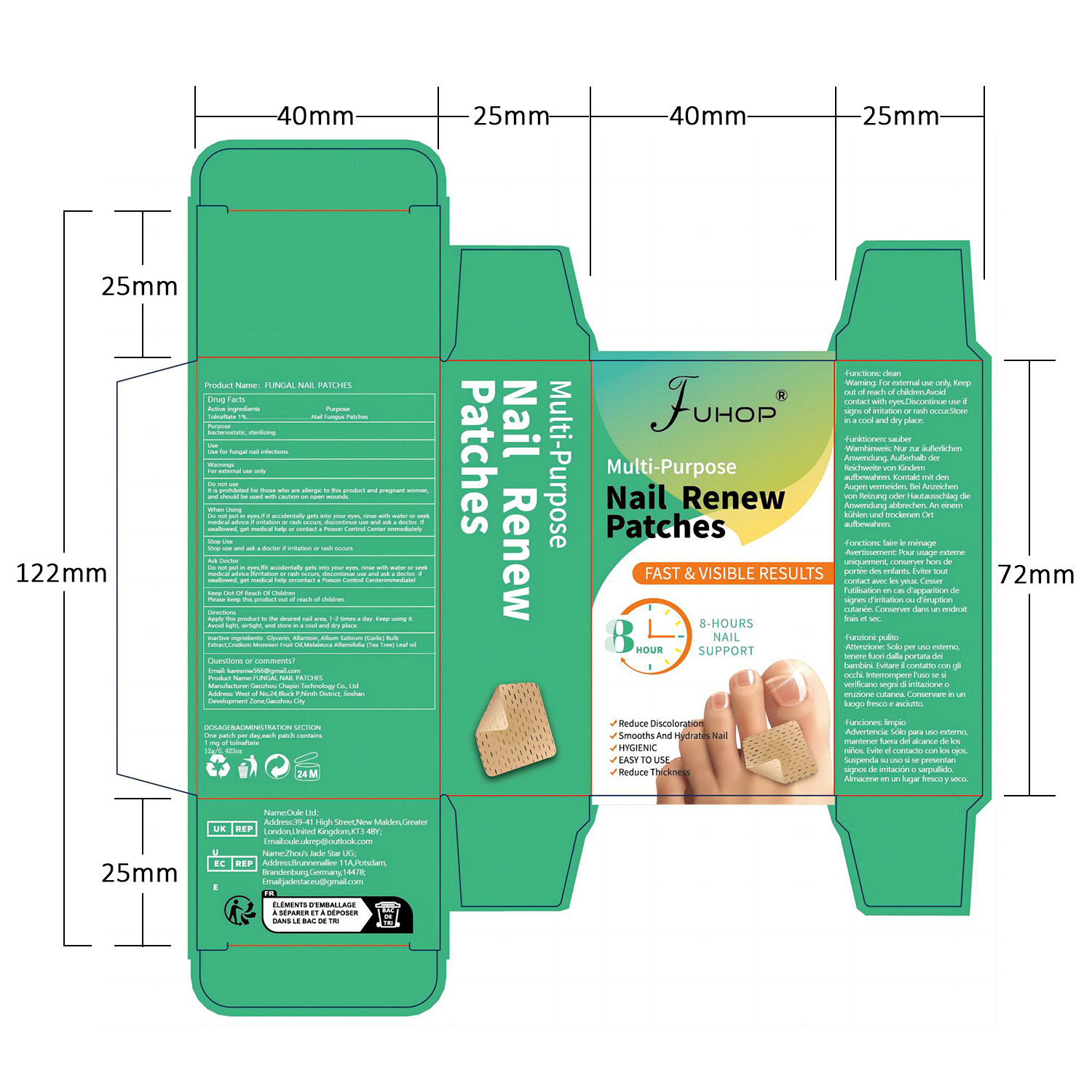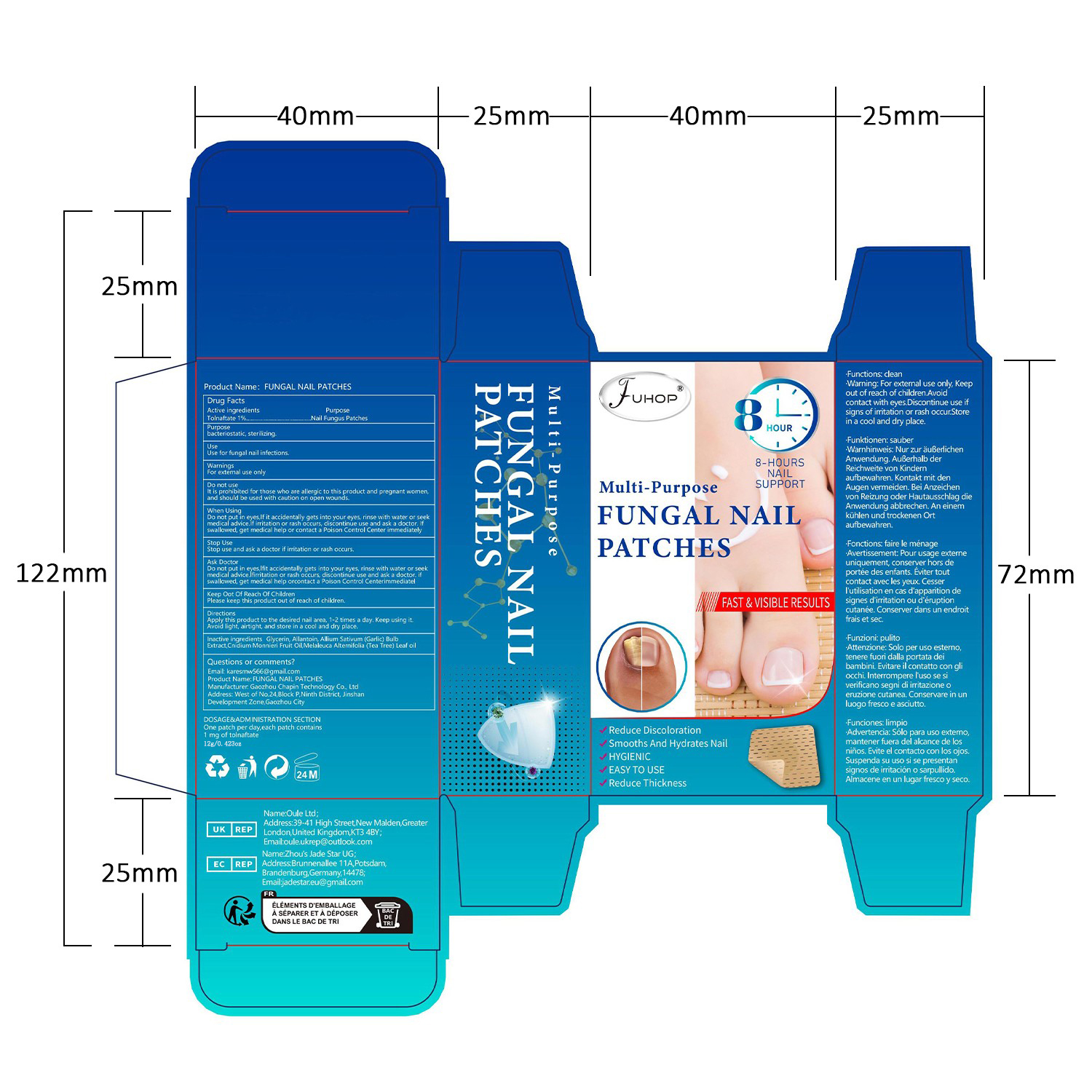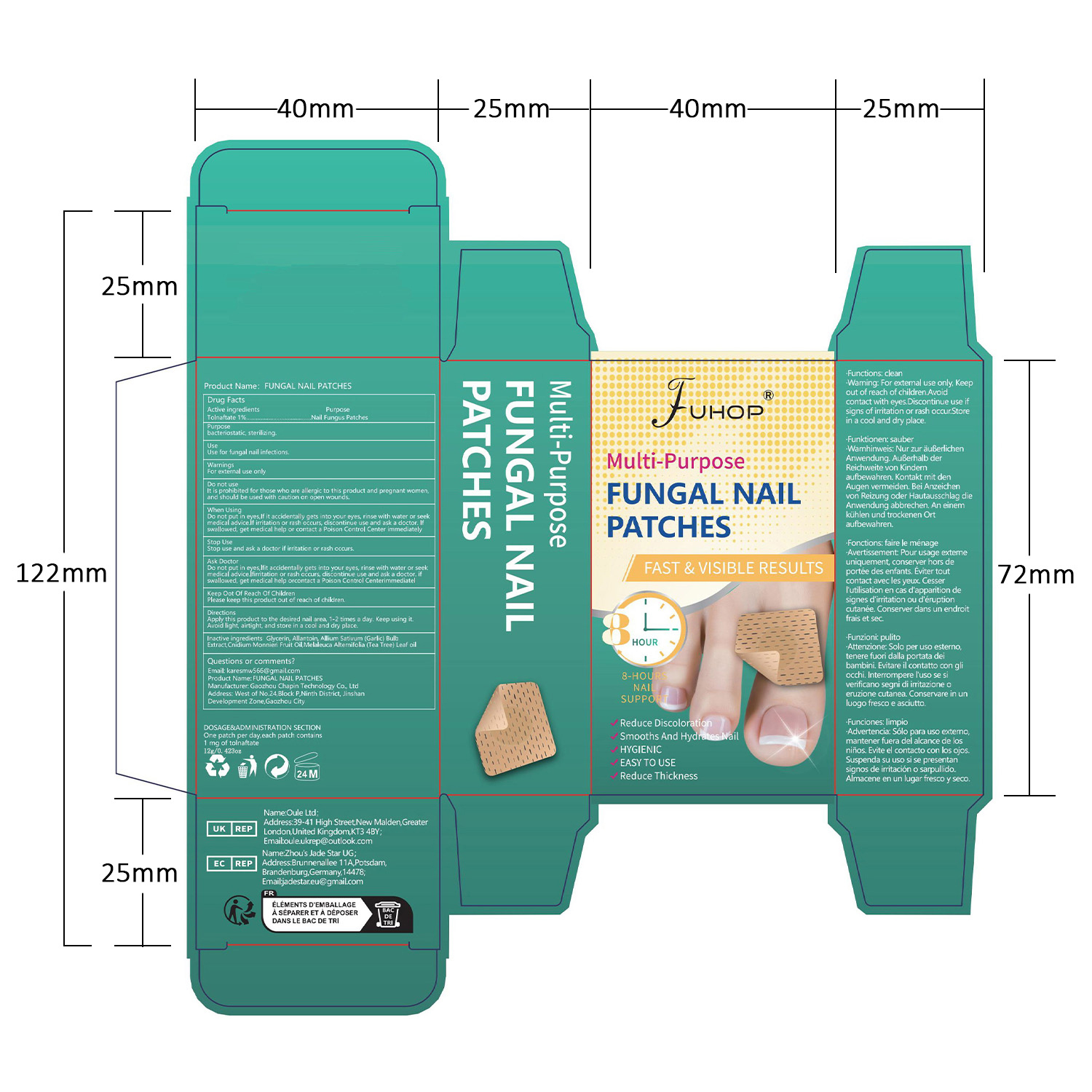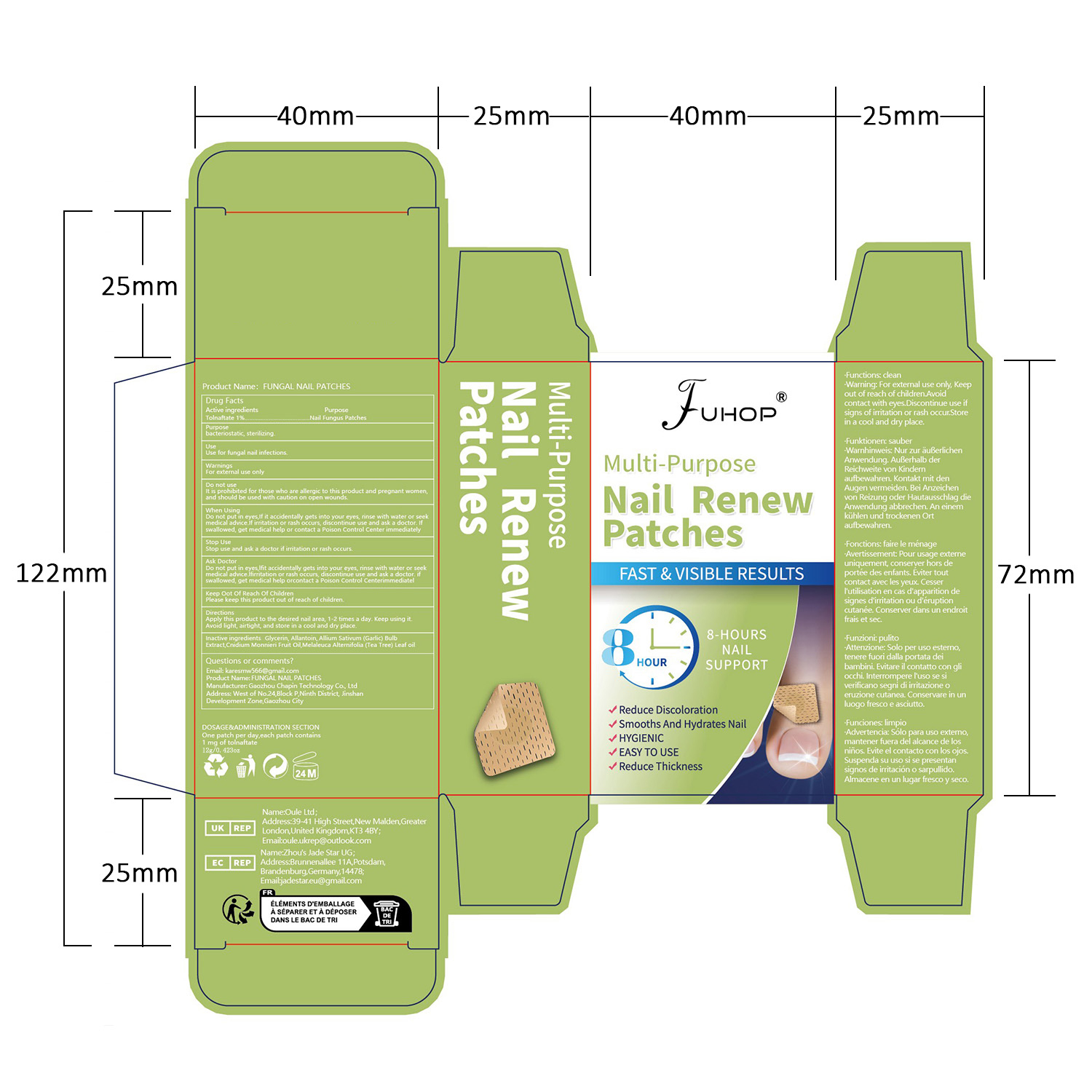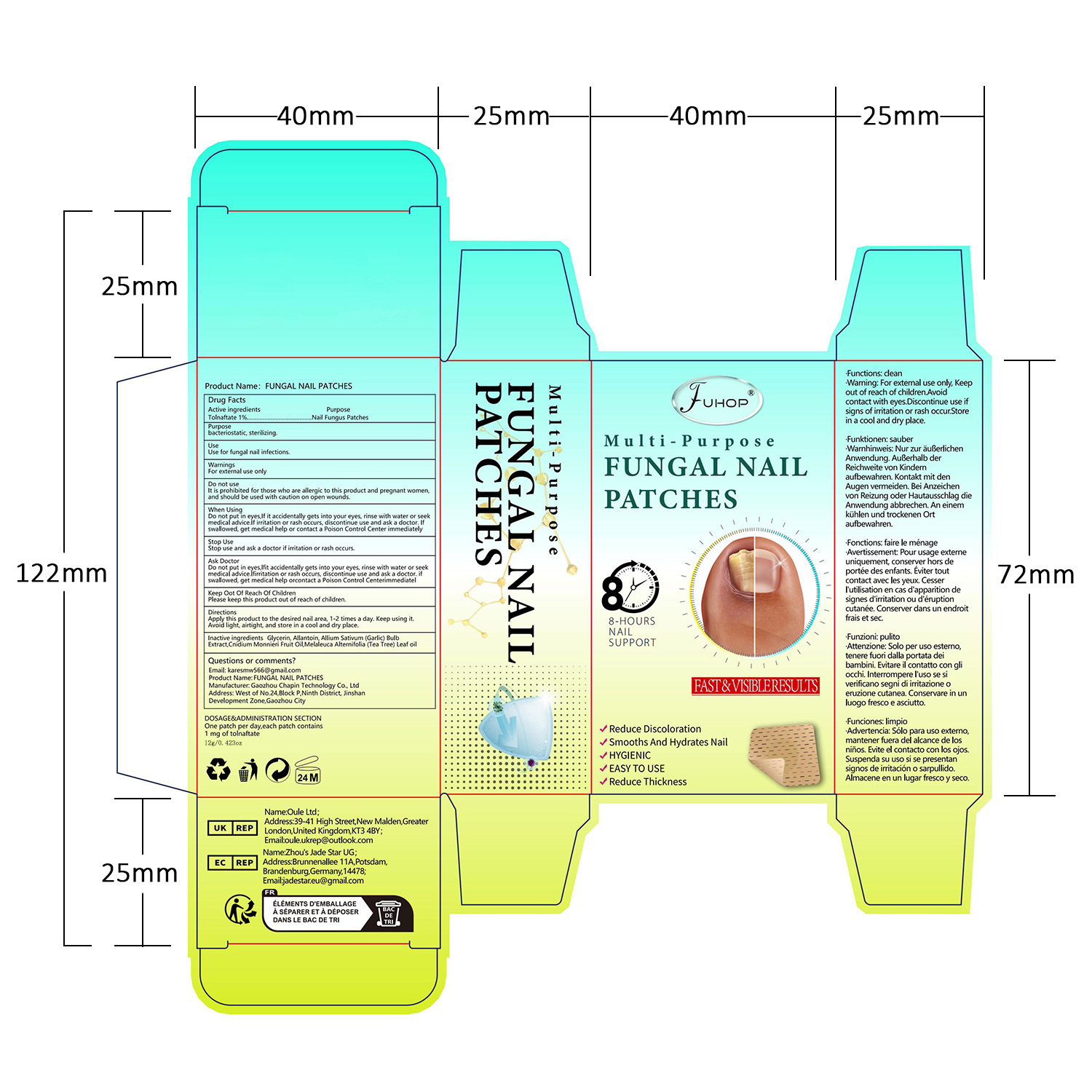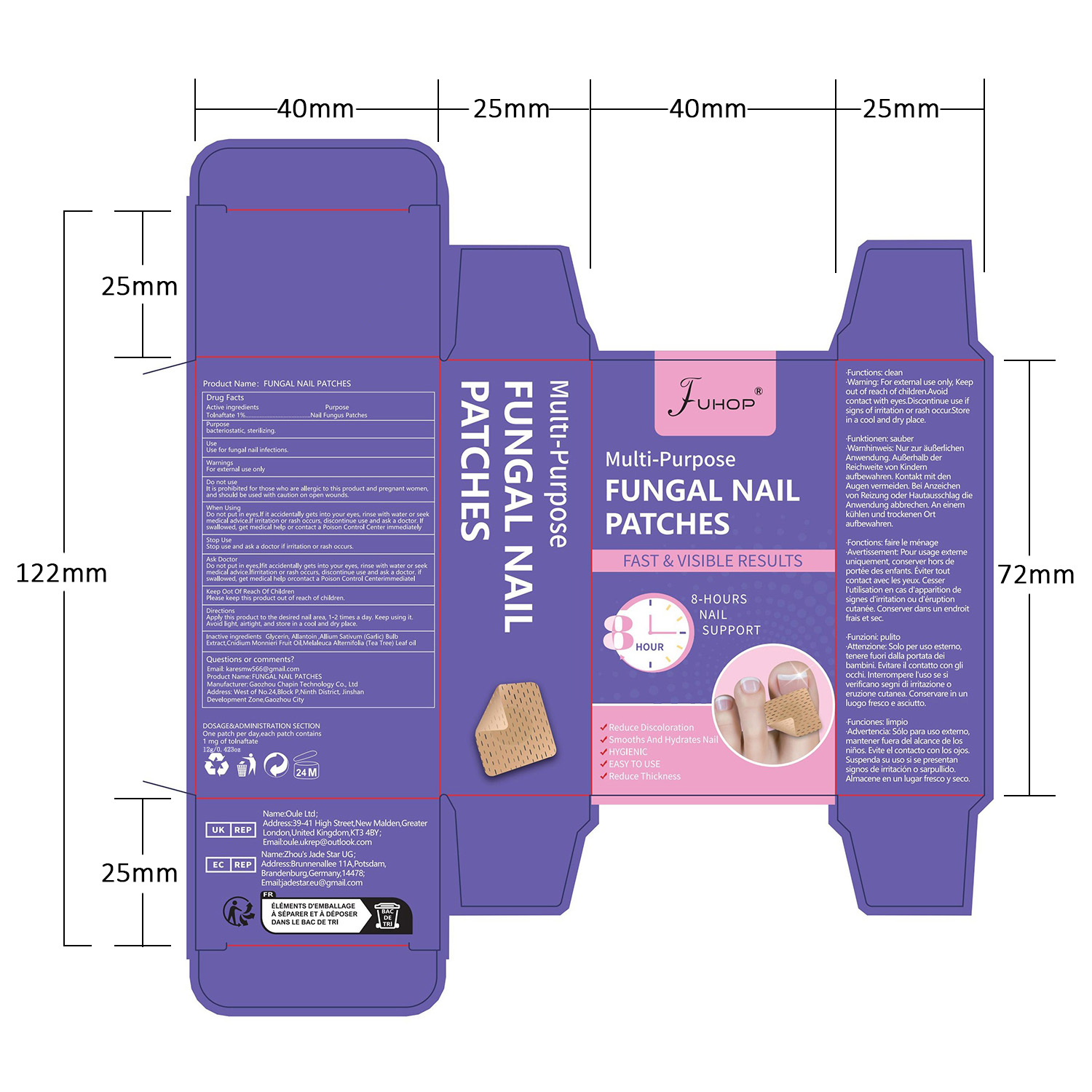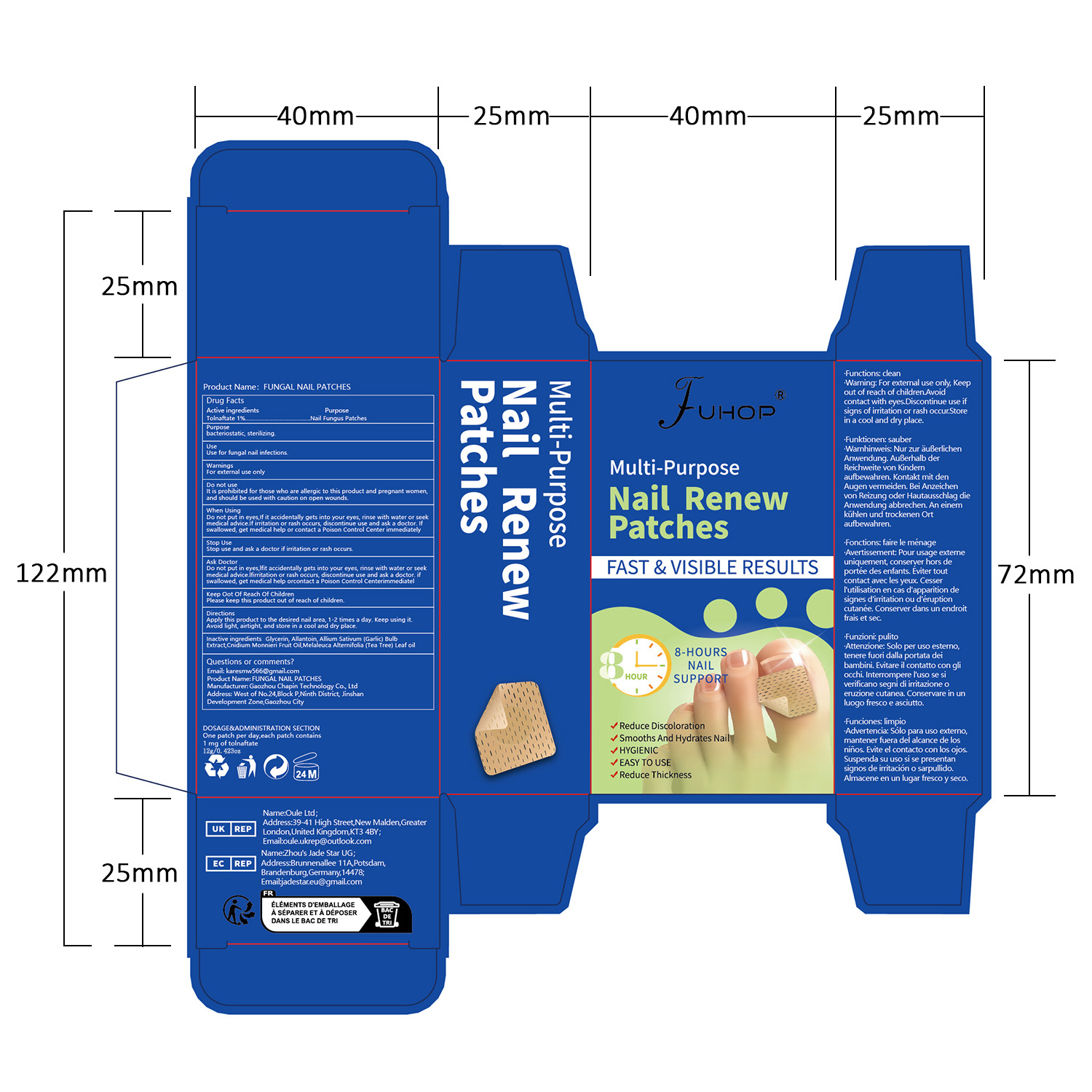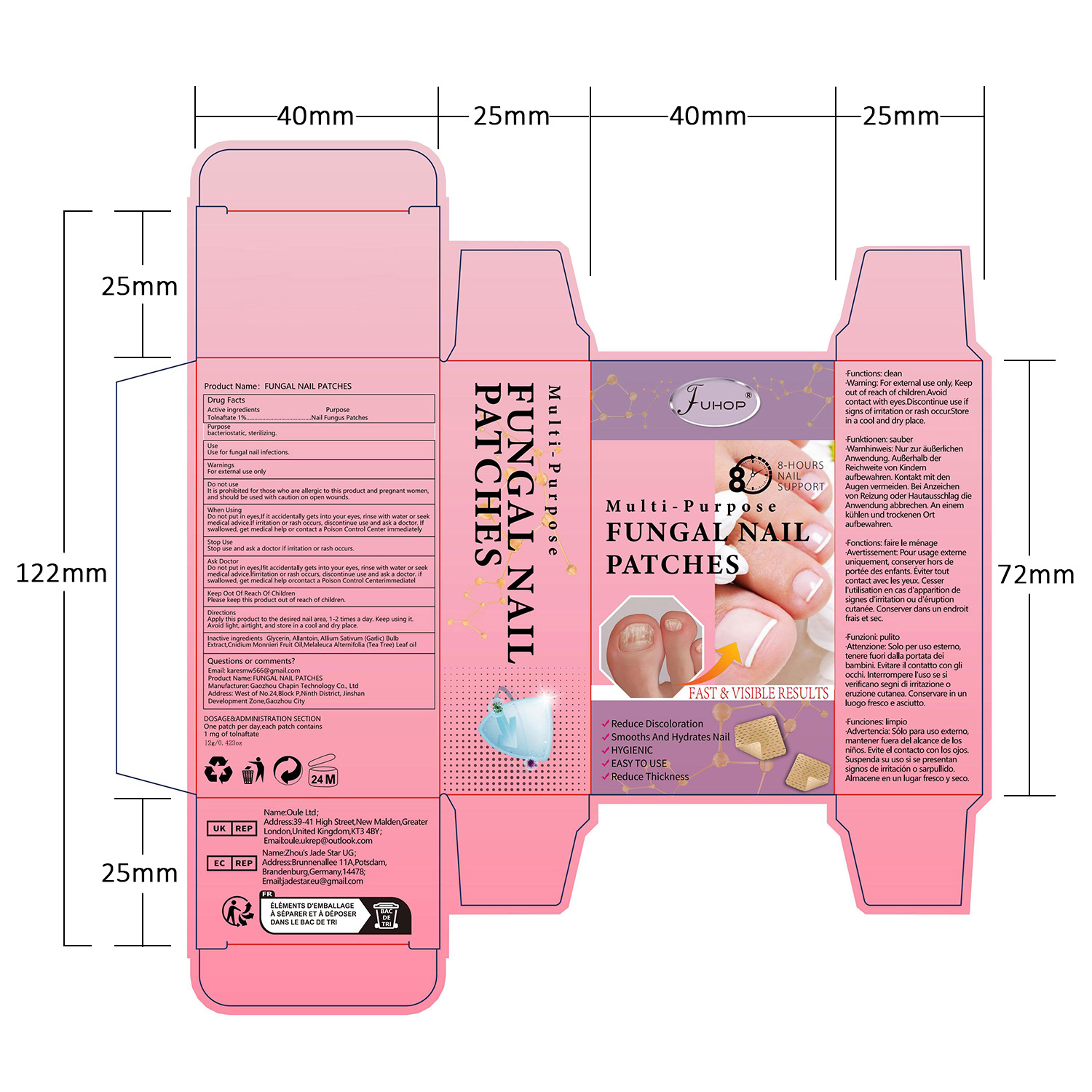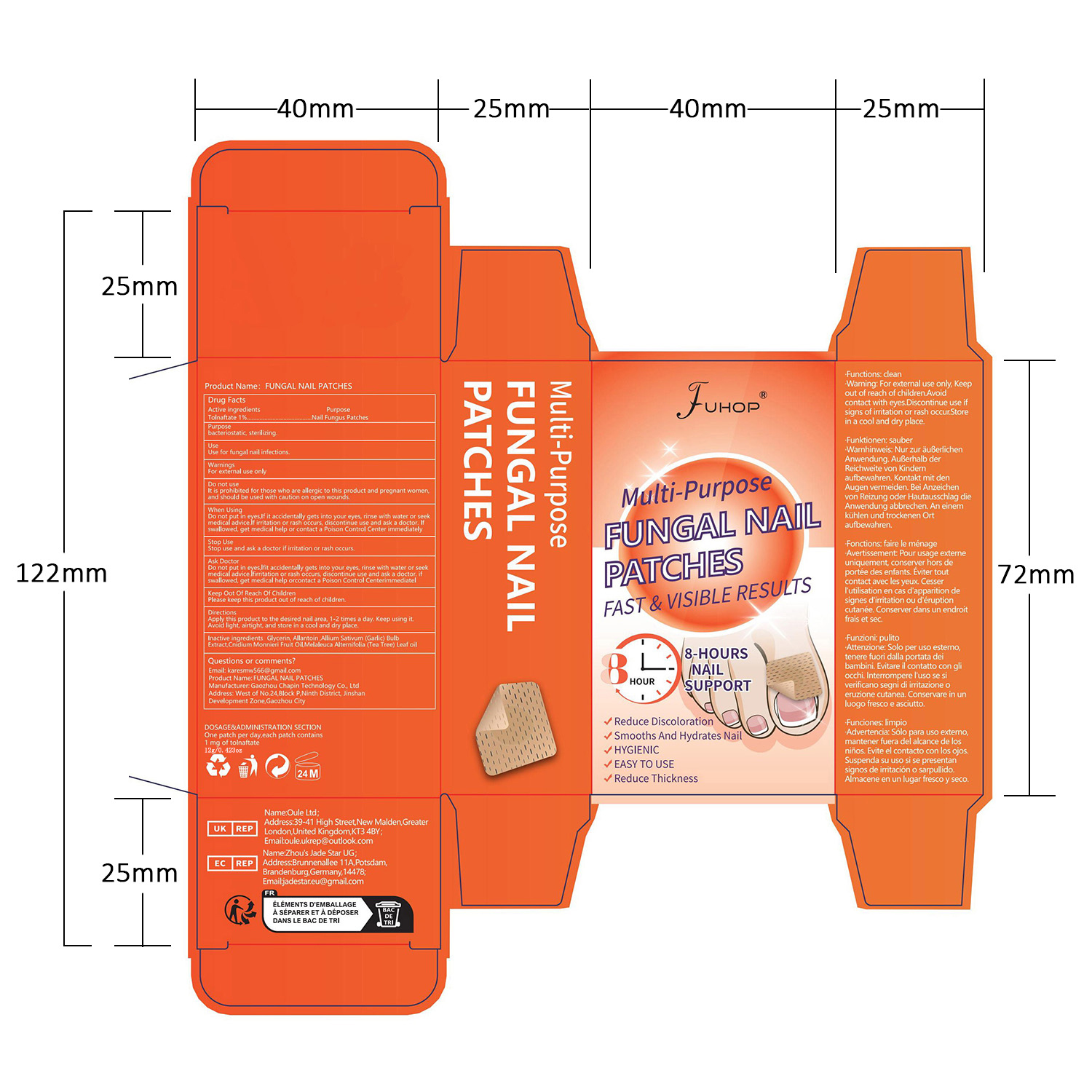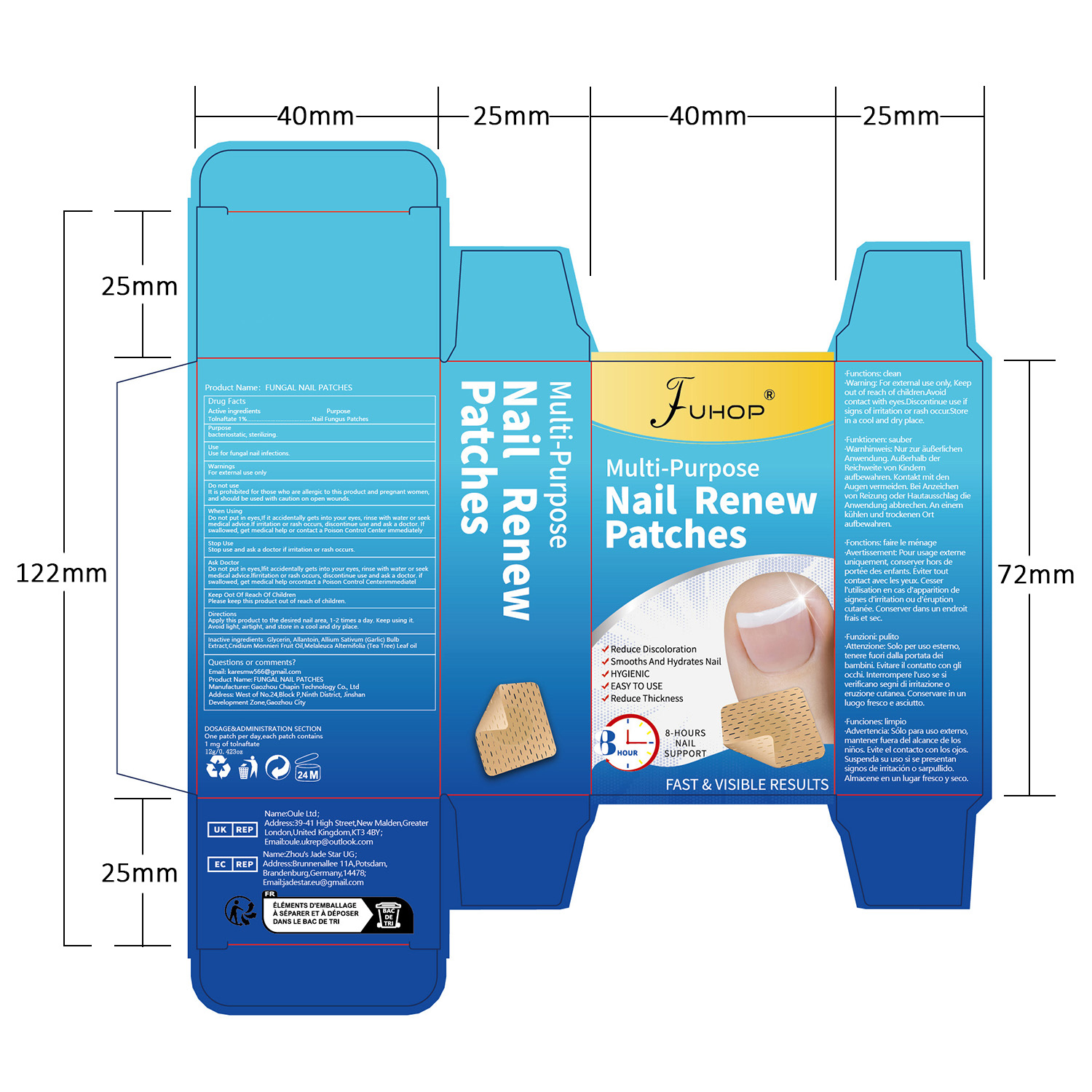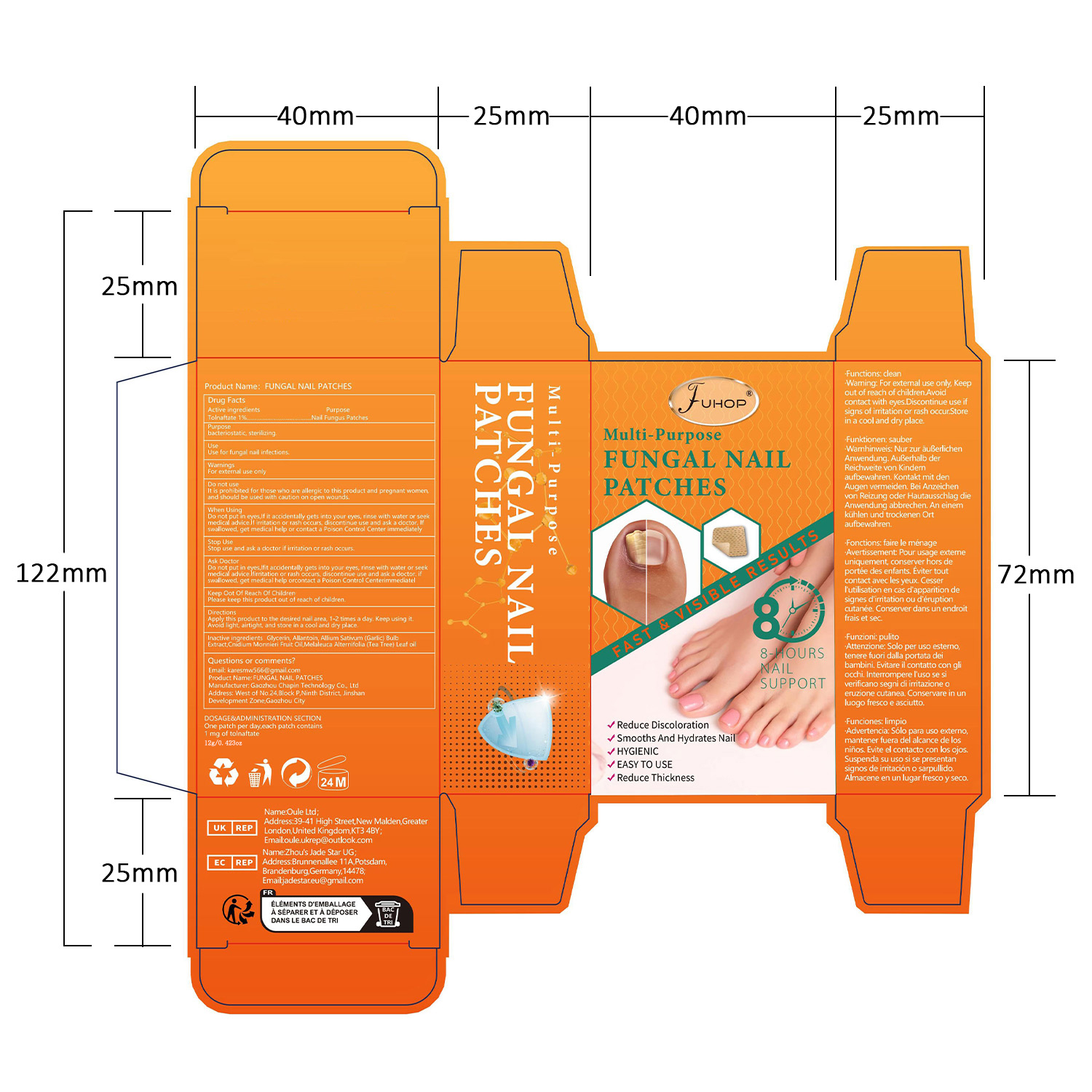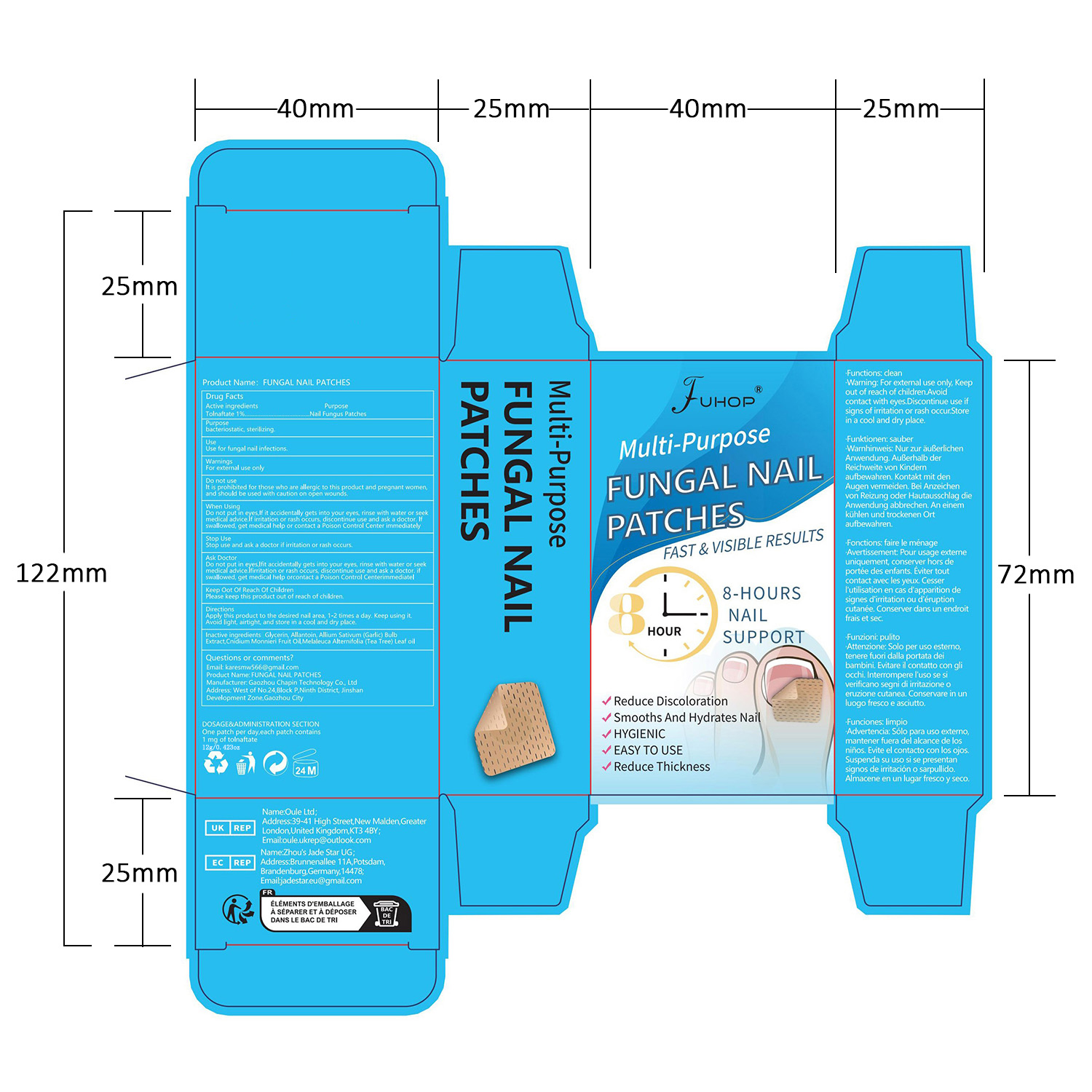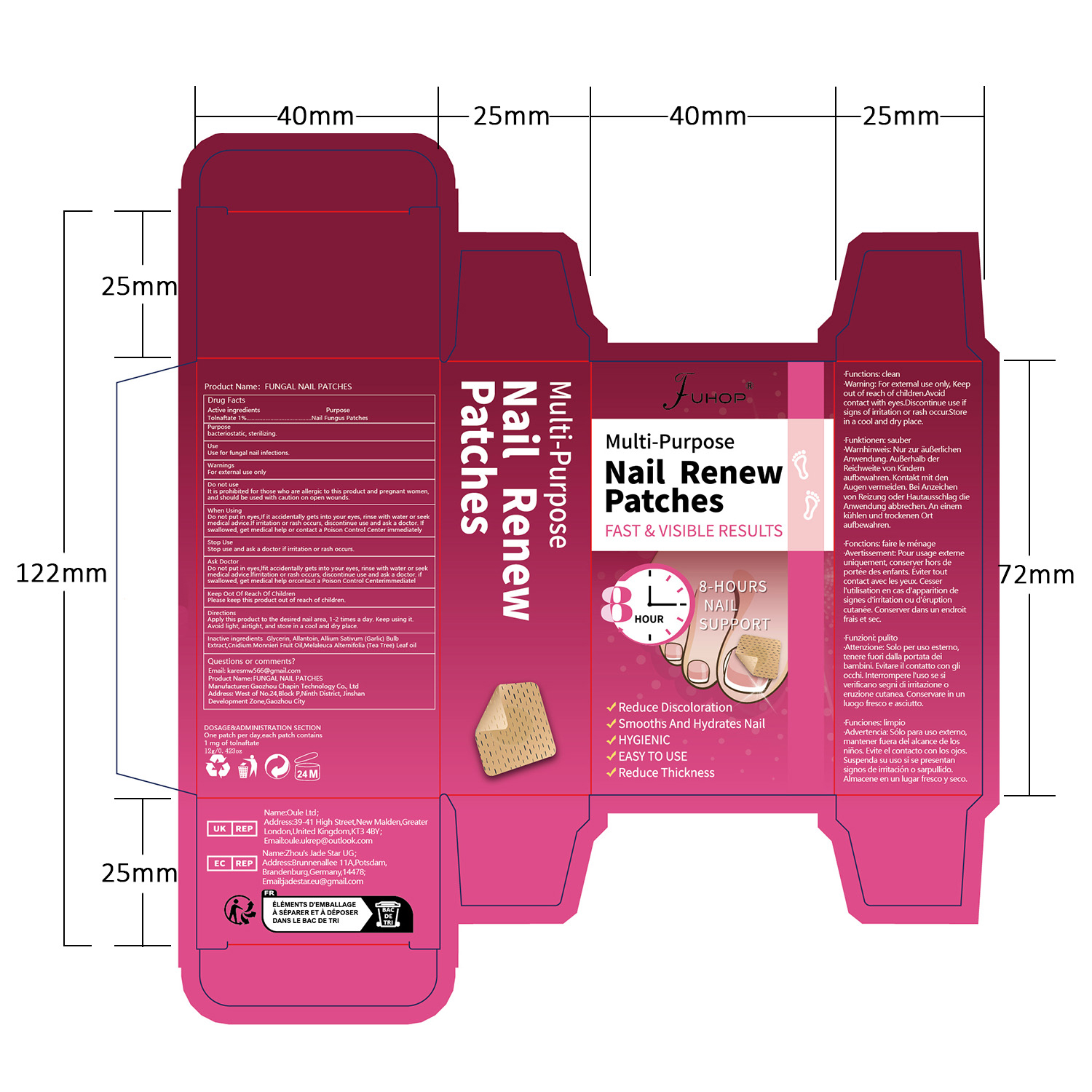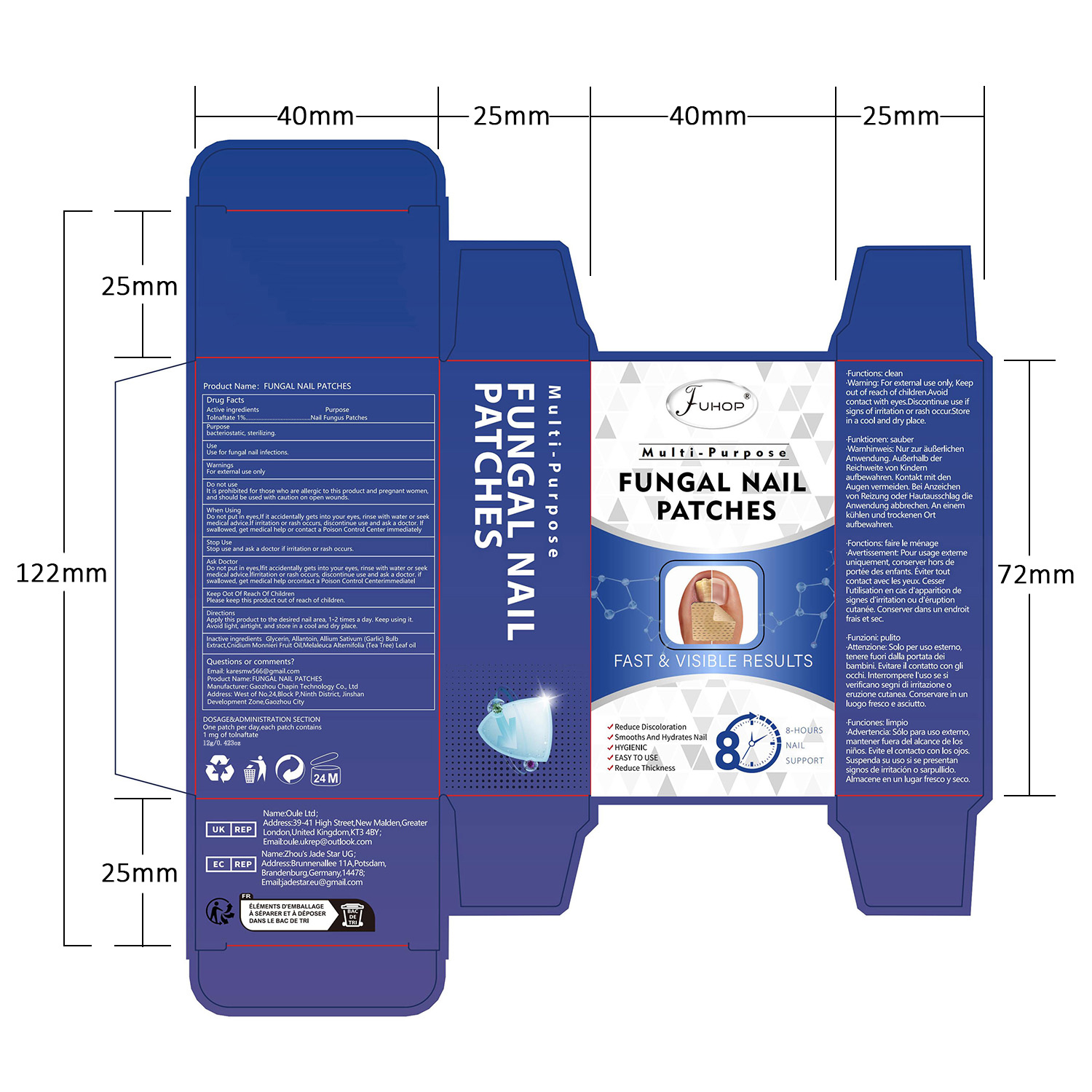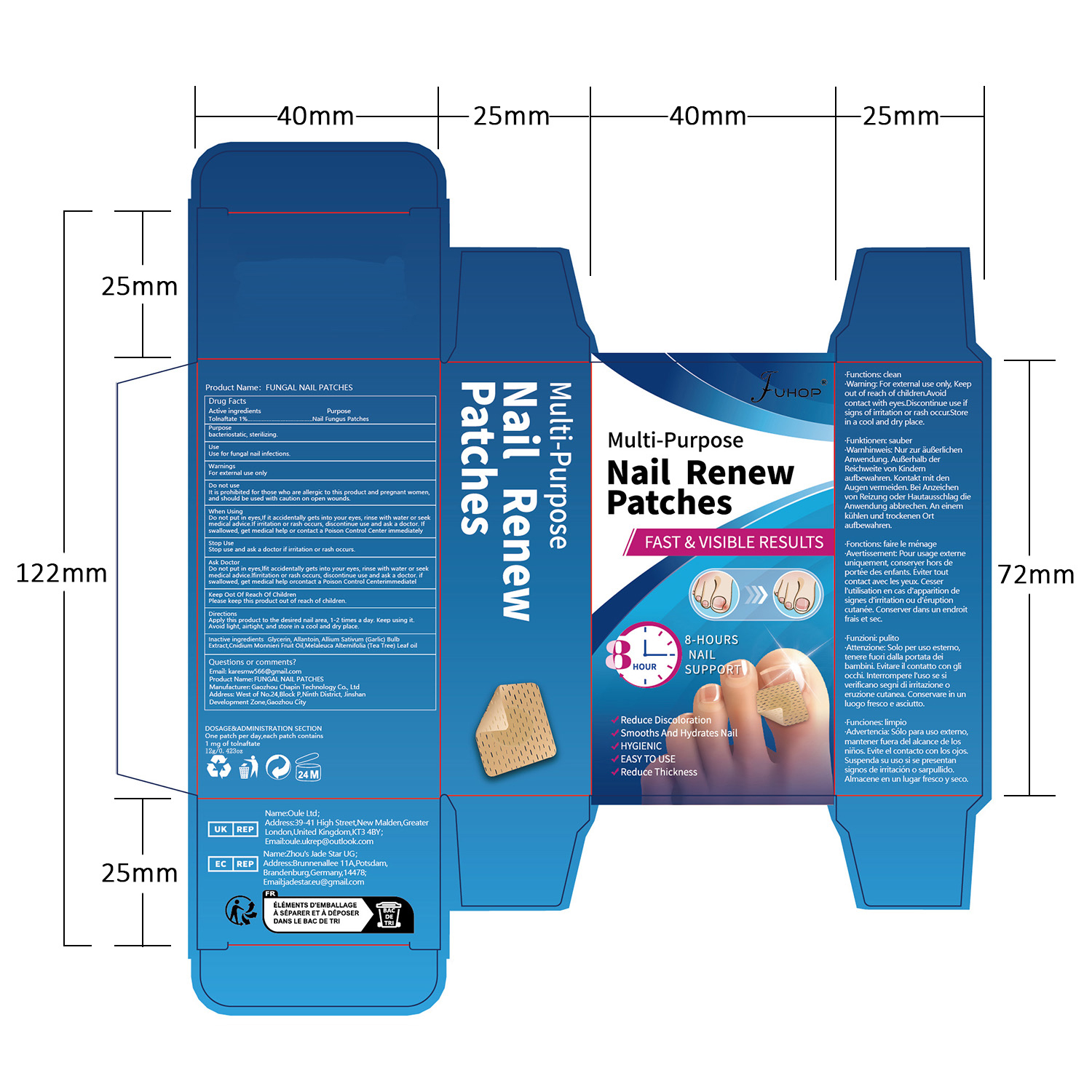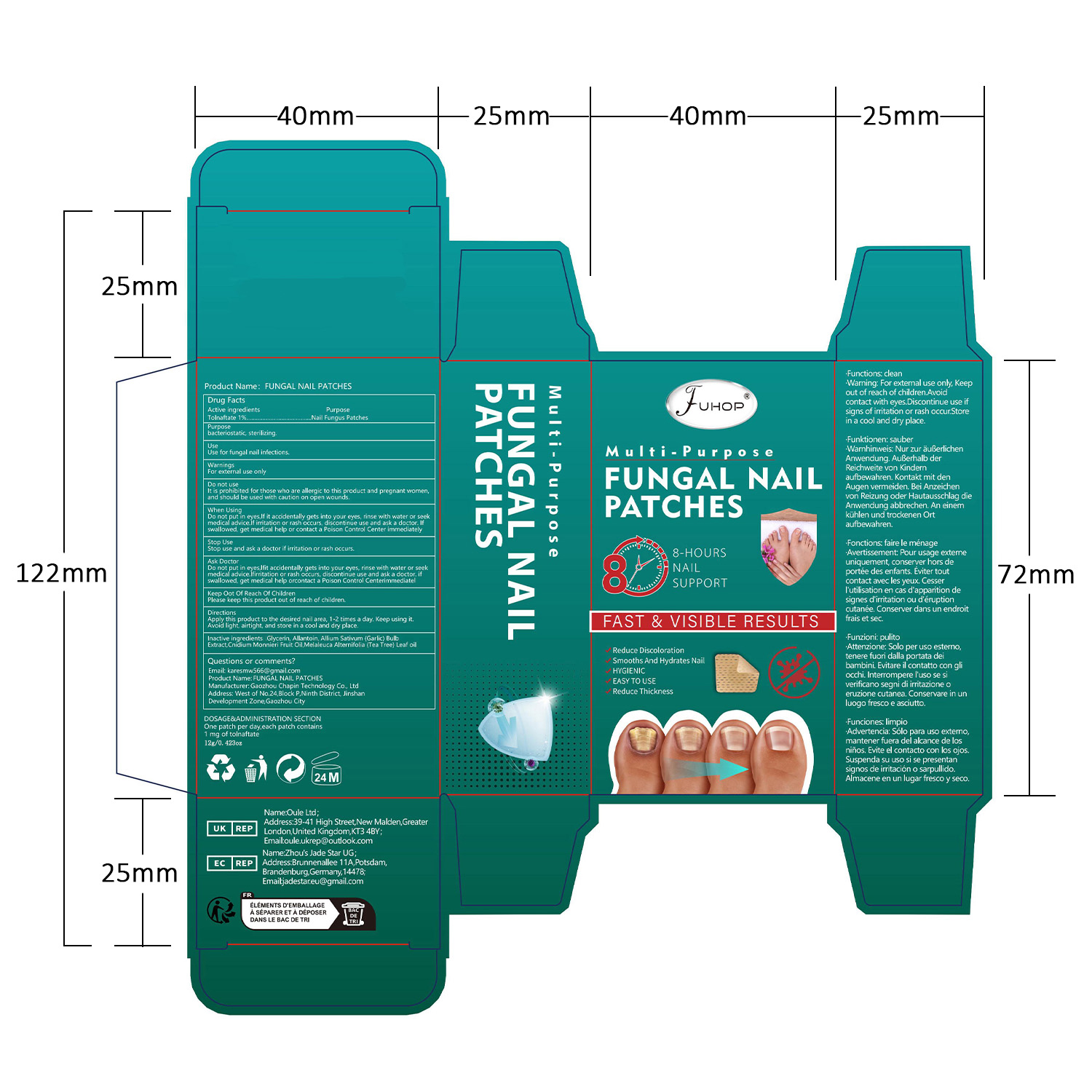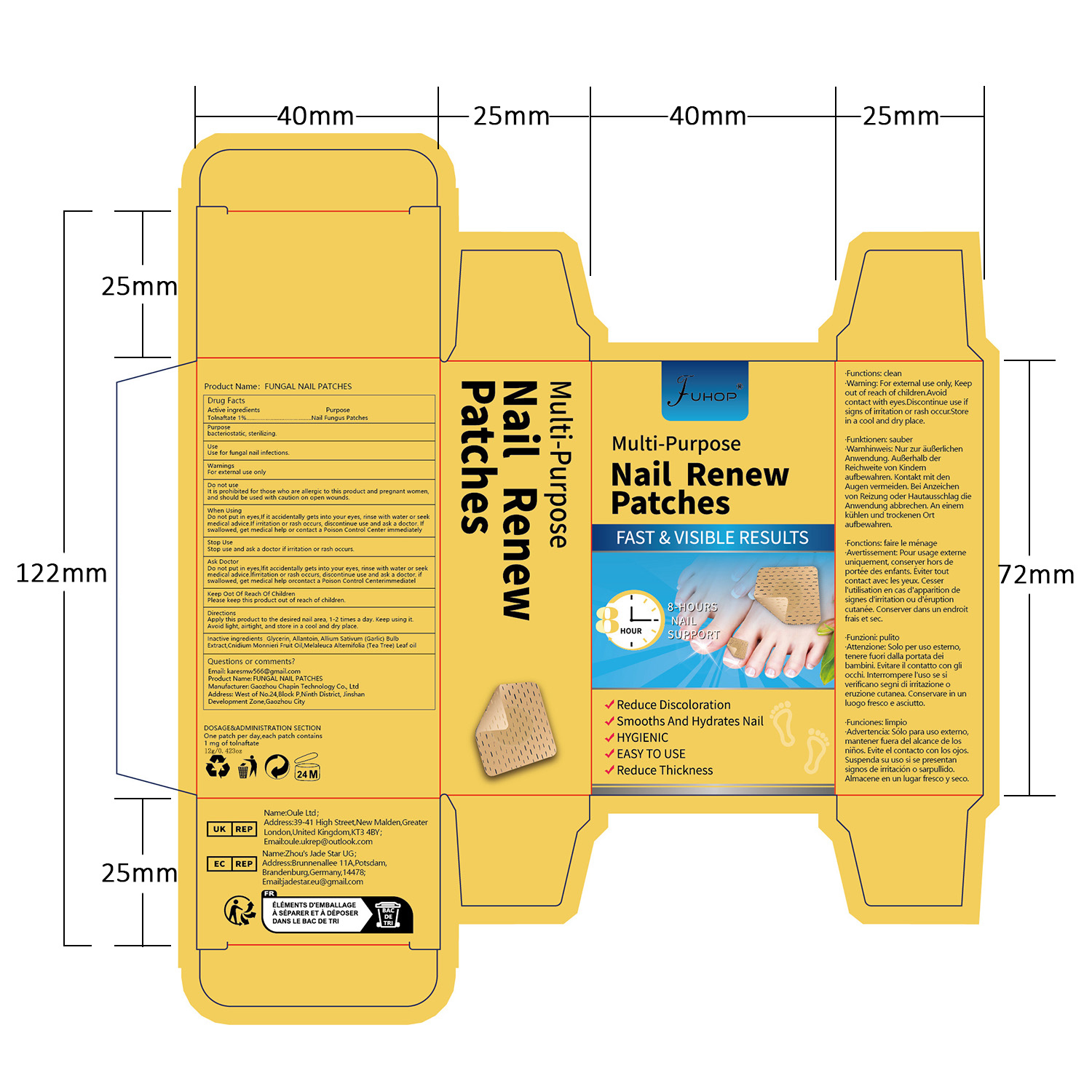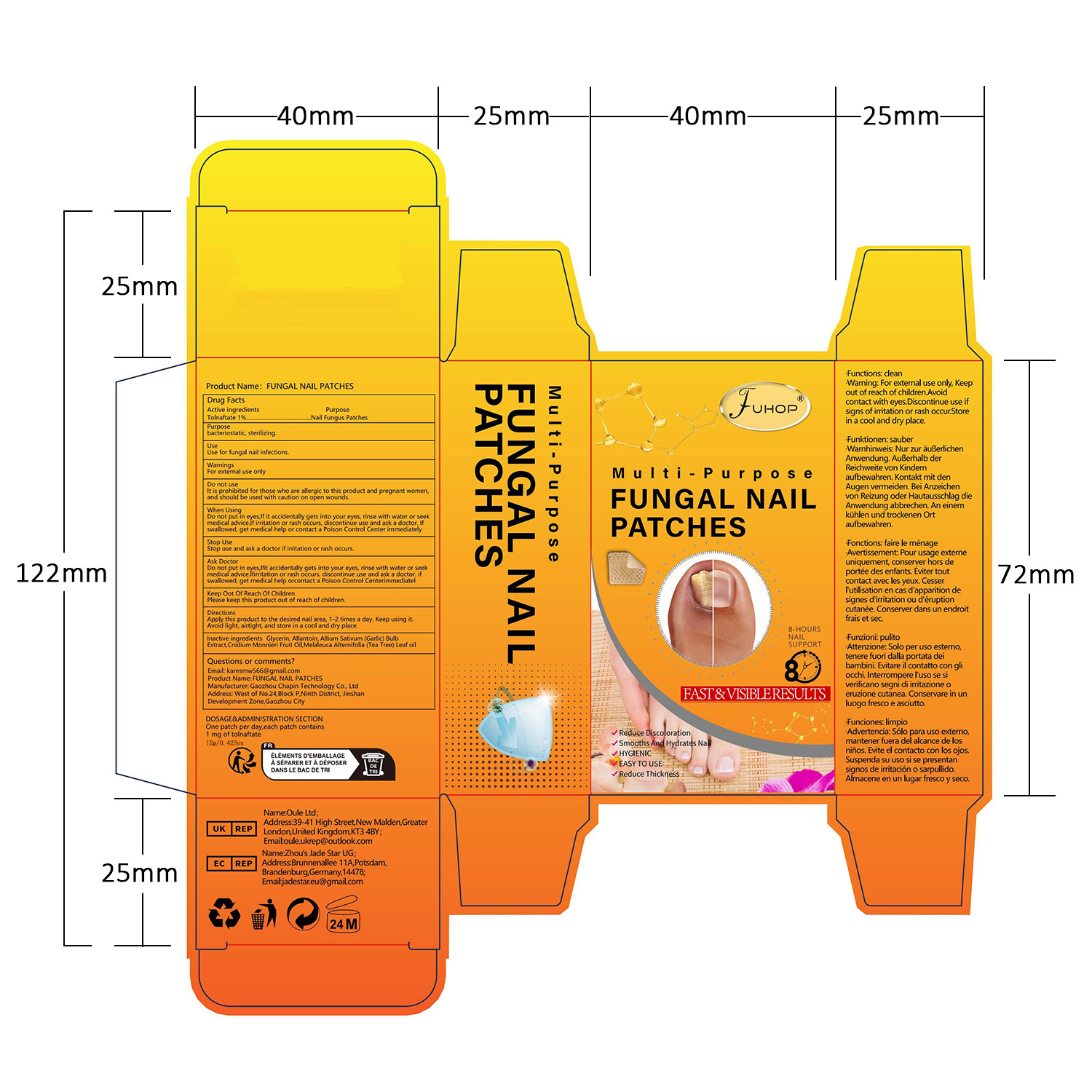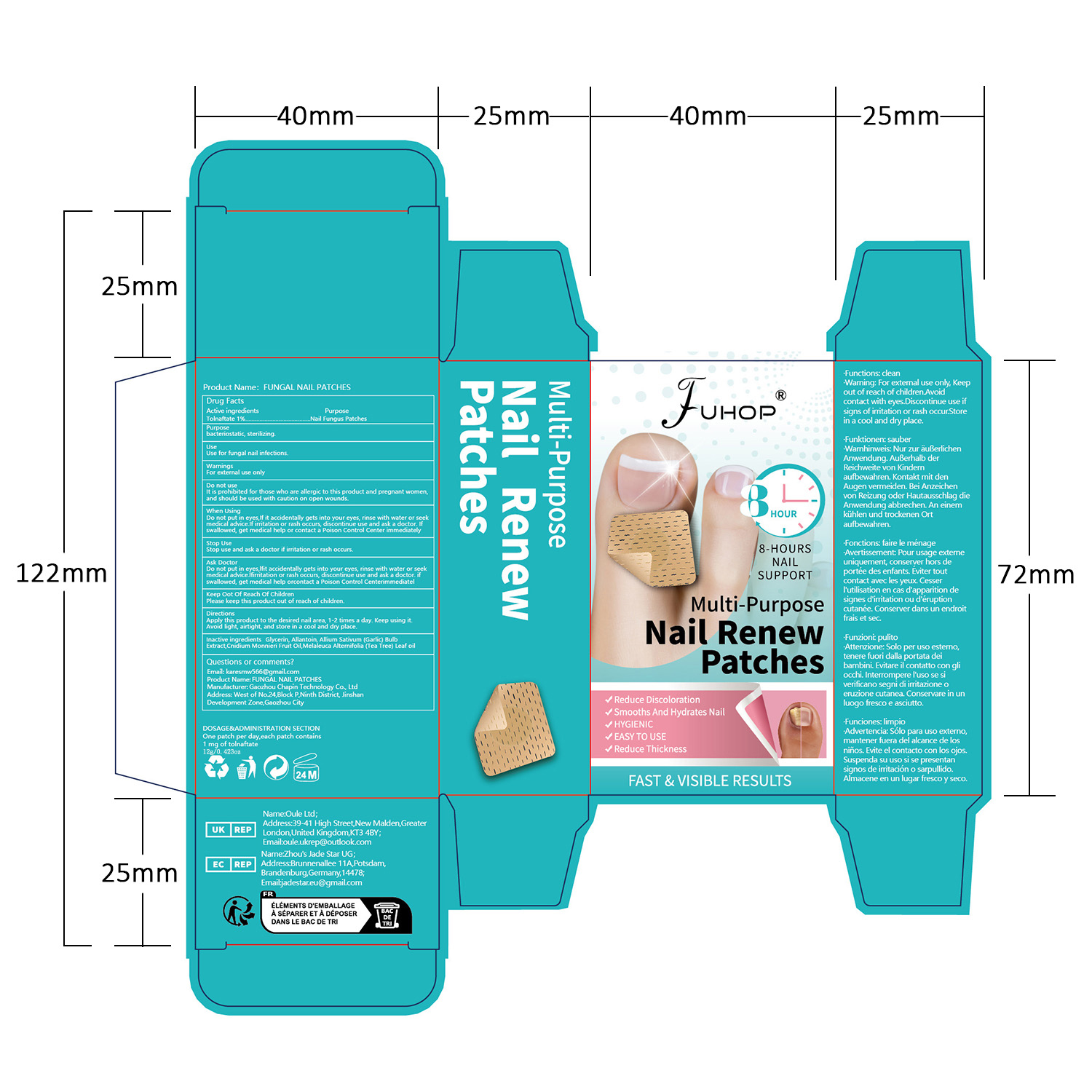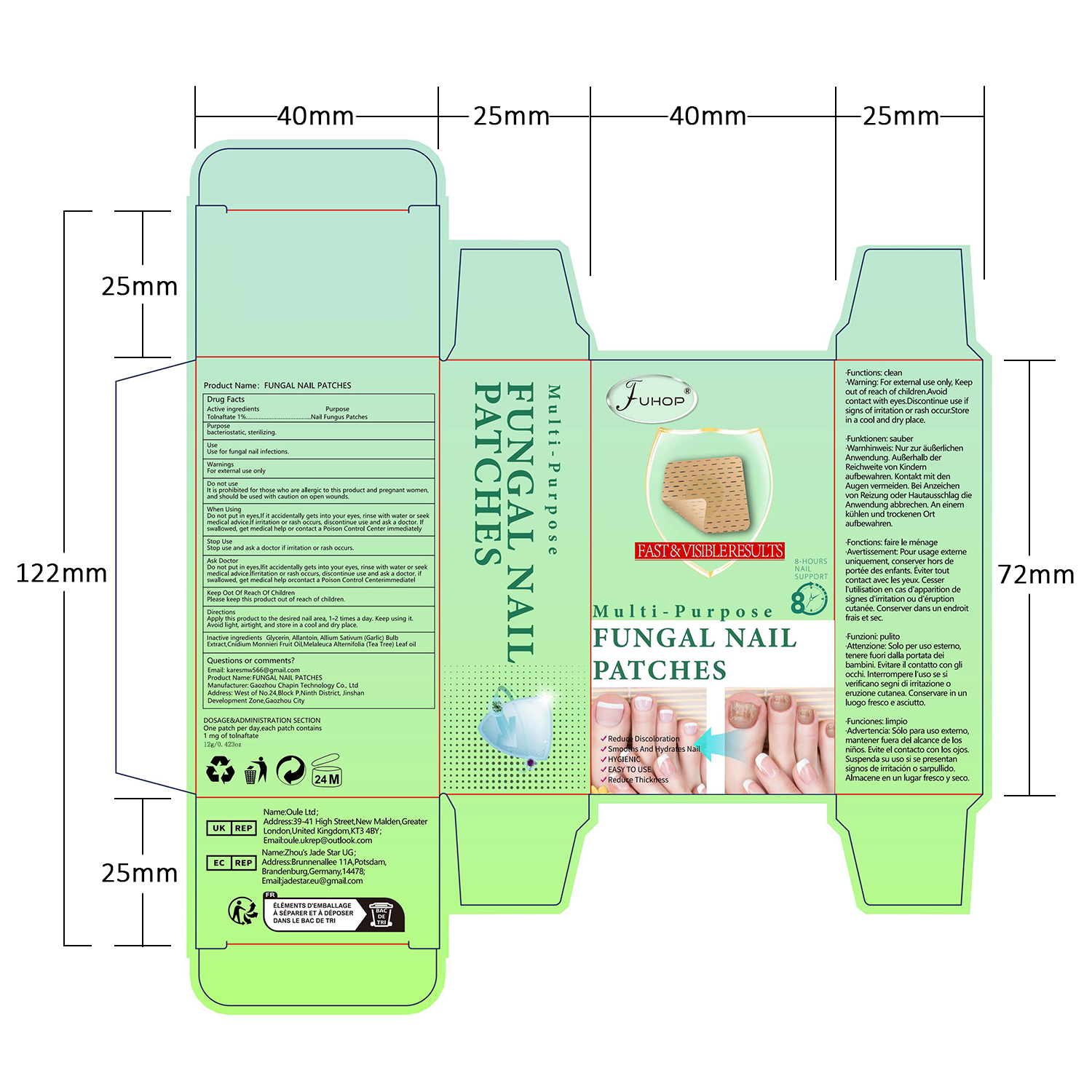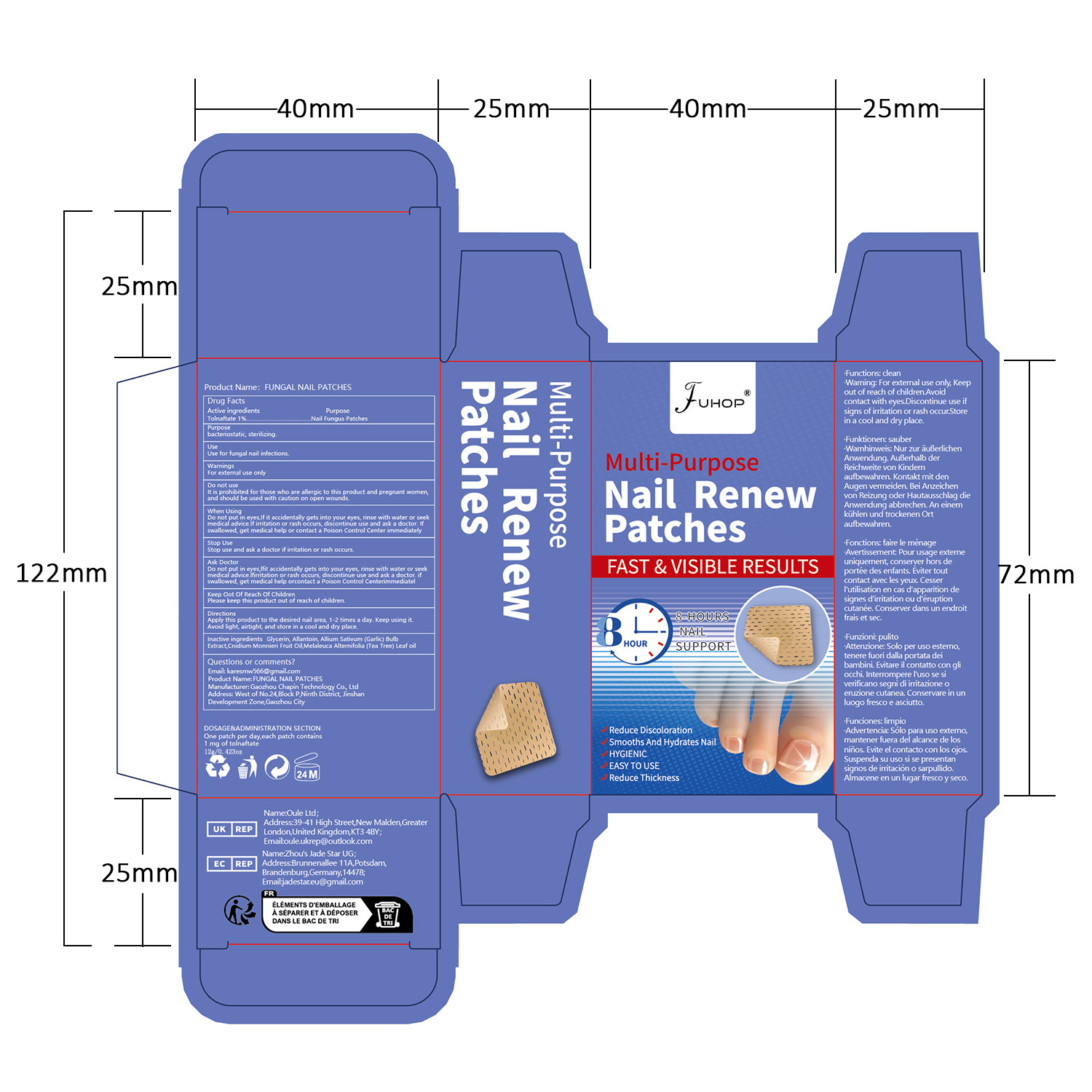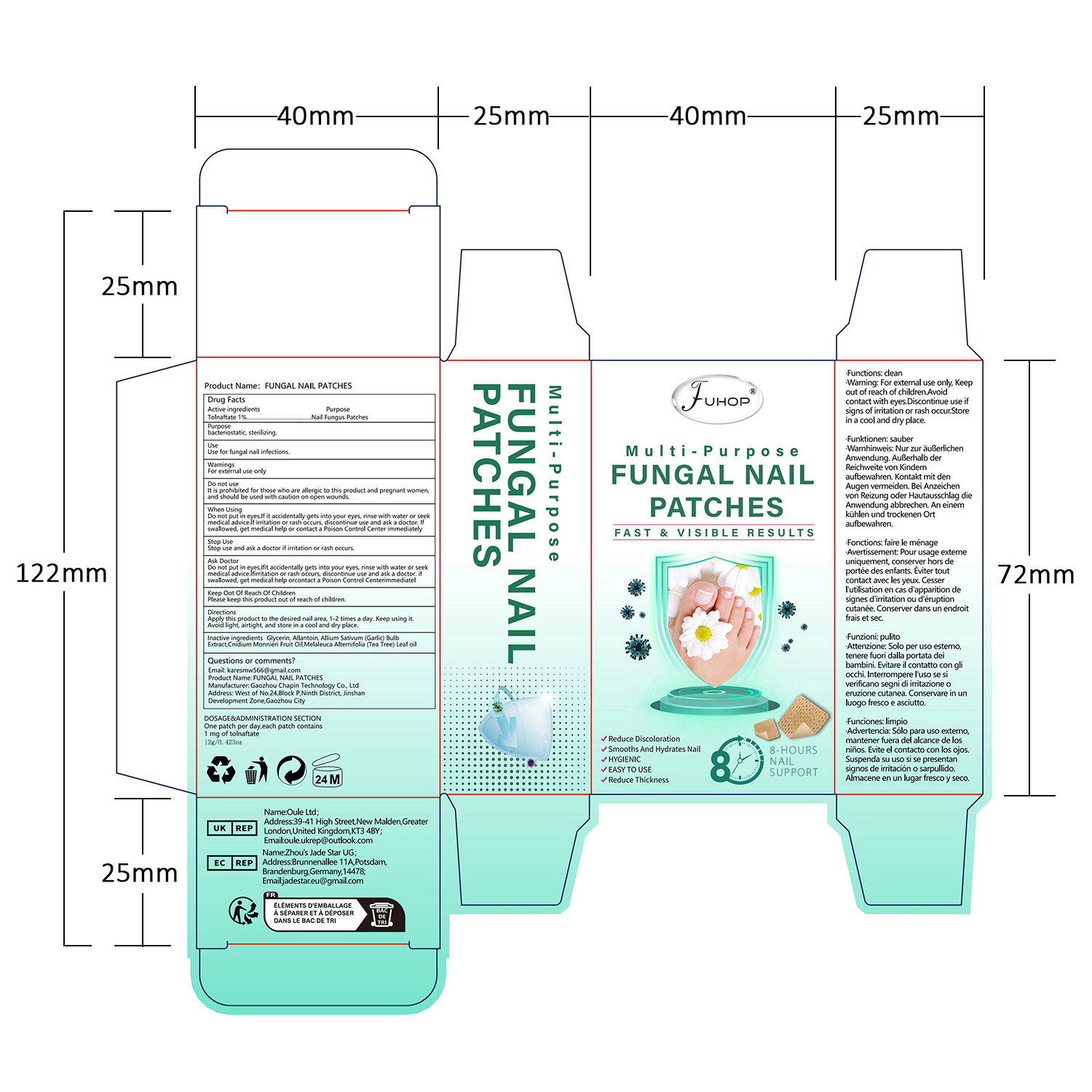 DRUG LABEL: FUHOP Fungal Nail Patches
NDC: 84168-035 | Form: PATCH
Manufacturer: Gaozhou Chapin Technology Co., Ltd
Category: otc | Type: HUMAN OTC DRUG LABEL
Date: 20240707

ACTIVE INGREDIENTS: TOLNAFTATE 1 g/100 g
INACTIVE INGREDIENTS: GARLIC; MELALEUCA ALTERNIFOLIA (TEA TREE) LEAF OIL; ALLANTOIN; CNIDIUM MONNIERI FRUIT OIL; GLYCERIN

Active ingredients

Tolnaftate 1%

Purpose

bacteriostatic, sterilizing.

Use

Use for fungal nail infections.

Warnings

For external use only

Do not use

It is prohibited for those who are allergic to this product and pregnant women,and should be used with caution on open wounds.

When Using

Do not put in eves,lf it accidentally gets into your eyes, rinse with water or seek medical advice,f irritation or rash occurs, discontinye use and ask a doctor. lf swallowed, get medical help or contact a Poison Control Center immediately

Stop Use

Stop use and ask a doctor if irritation or rash occurs.

Ask Doctor

Do not put in eves,lfit accidentally gets into your eyes, rinse with water or seekmedical advice.lfirritation or rash occurs, discontinue use and ask a doctor. if swallowed, get medical help orcontact a Poison Control Centerimmediatel

Keep Out Of Reach Of Children

Please keep this product out of reach of children.

Inactive ingredients

Glycerin, Alantoin,Alium Sativum (Garlic) Bulb Extract, Cnidium,Monnieri Fruit Oil,Melaleuca Alternifolia (Tea Tree) Leaf oi

DOSAGE & ADMINISTRATION SECTION

One patch per day, each patch contains 1 mg of tolnaftate